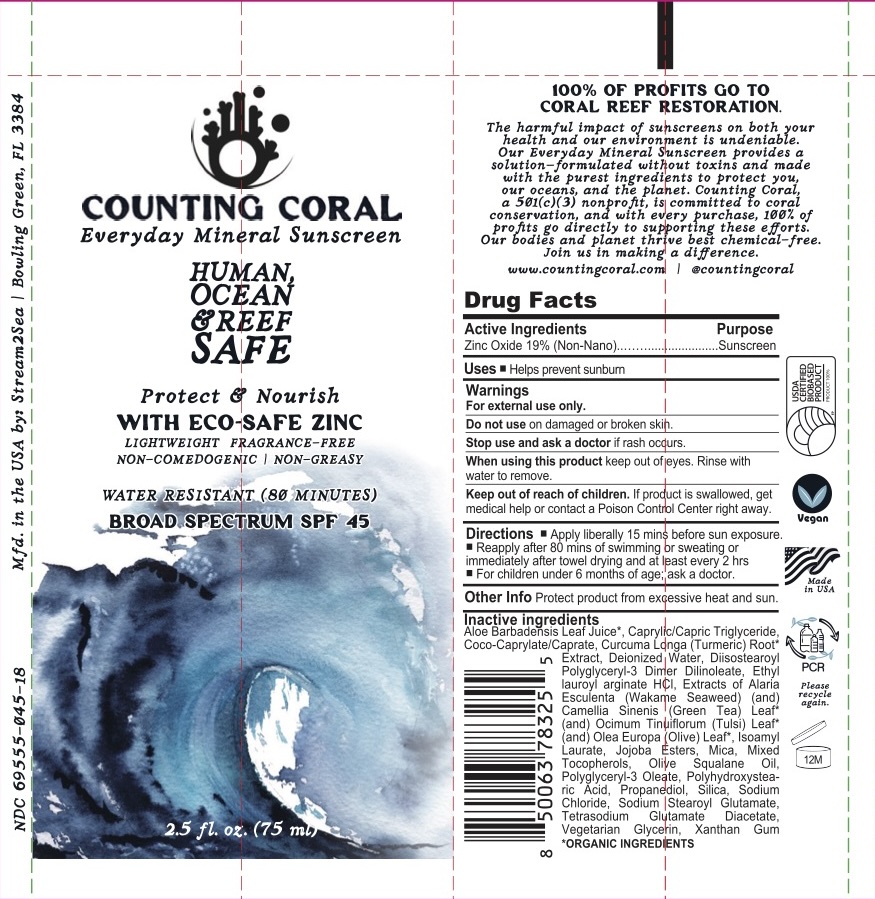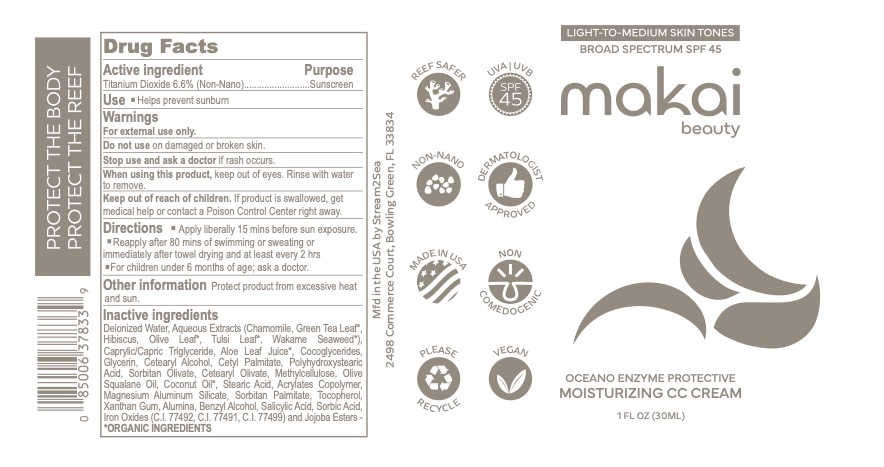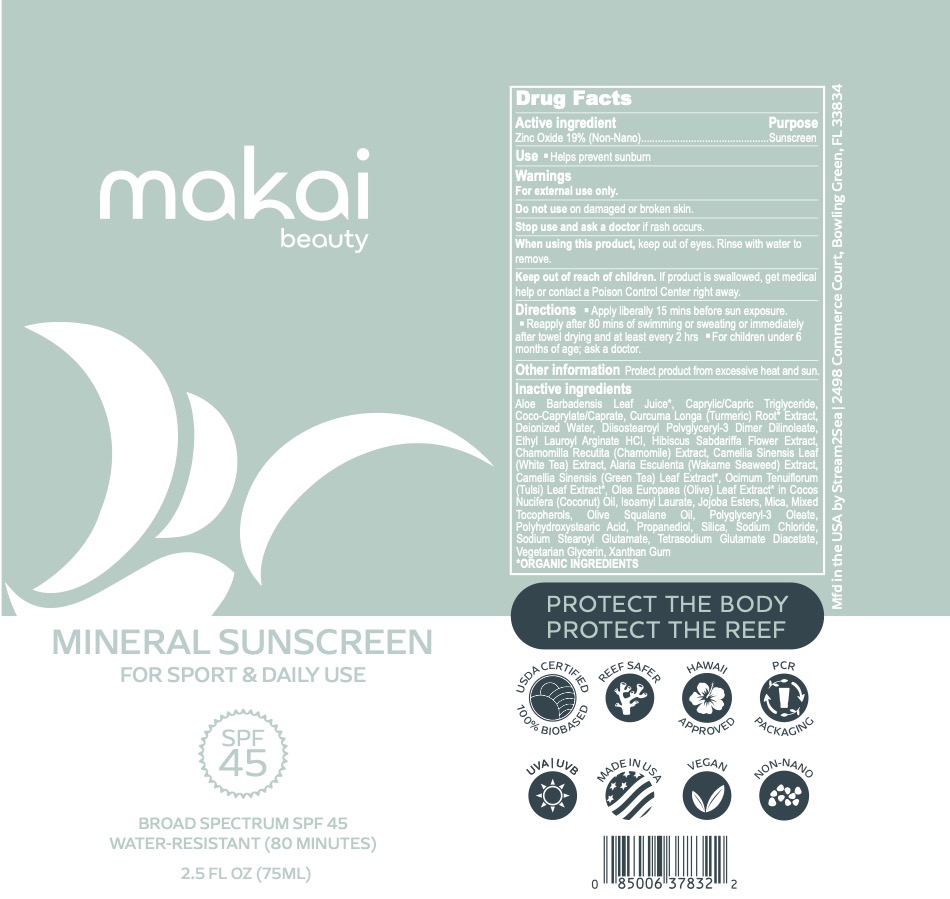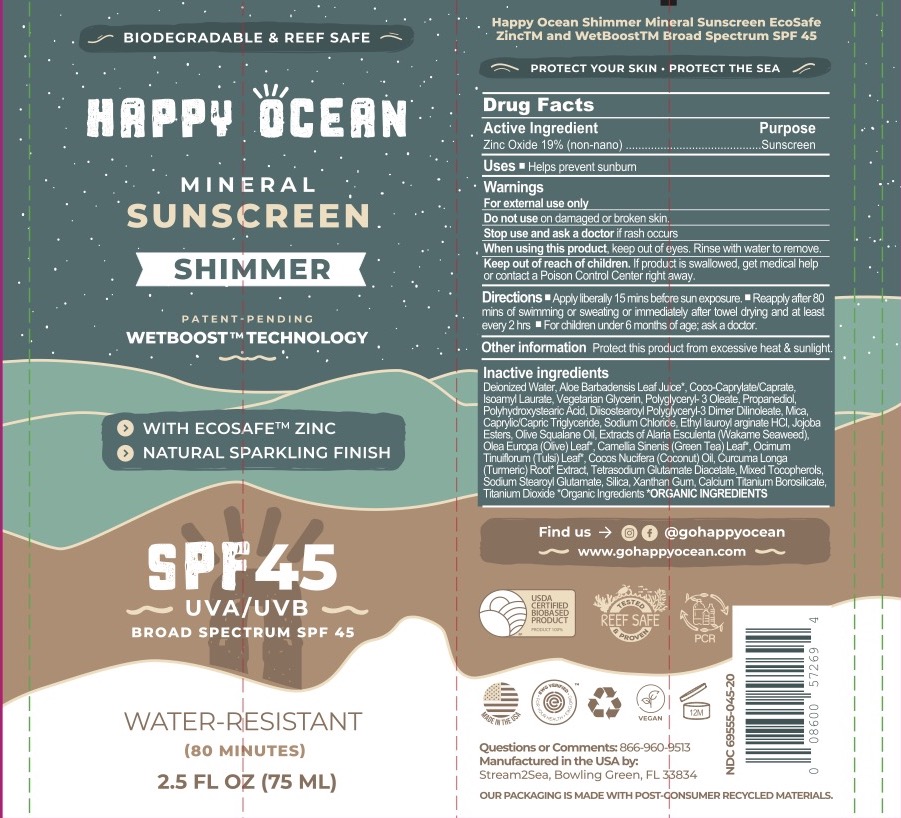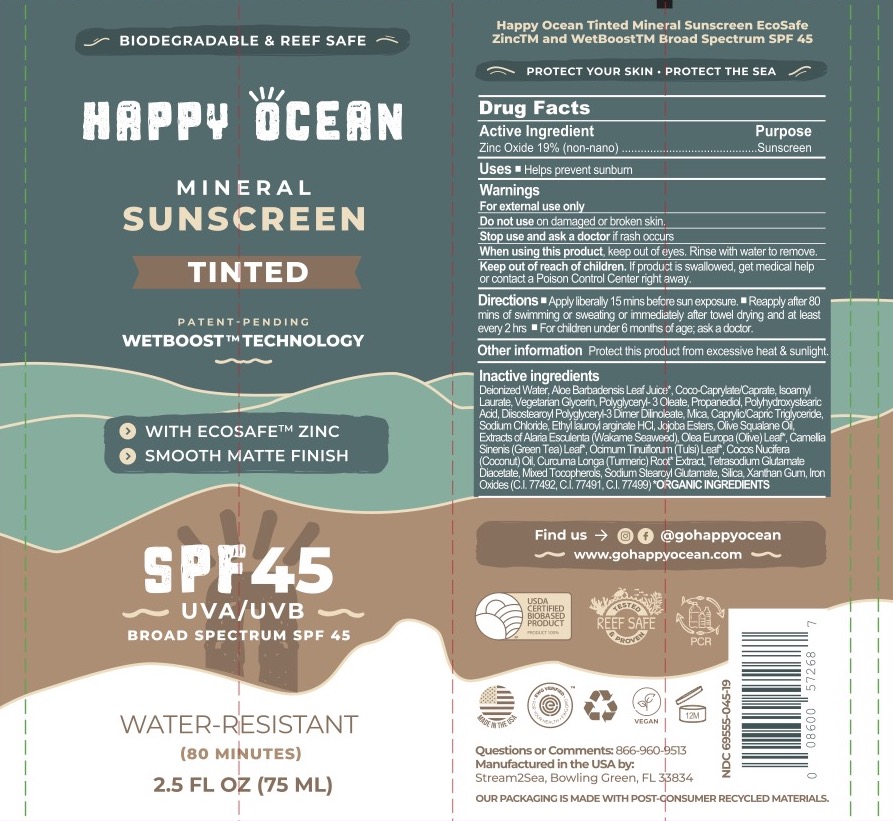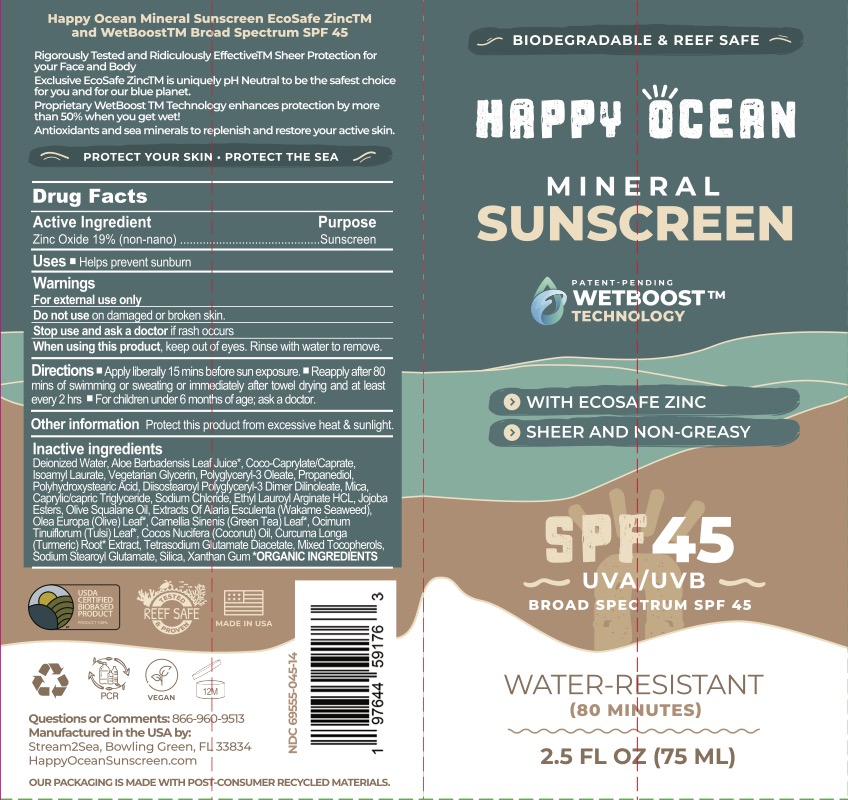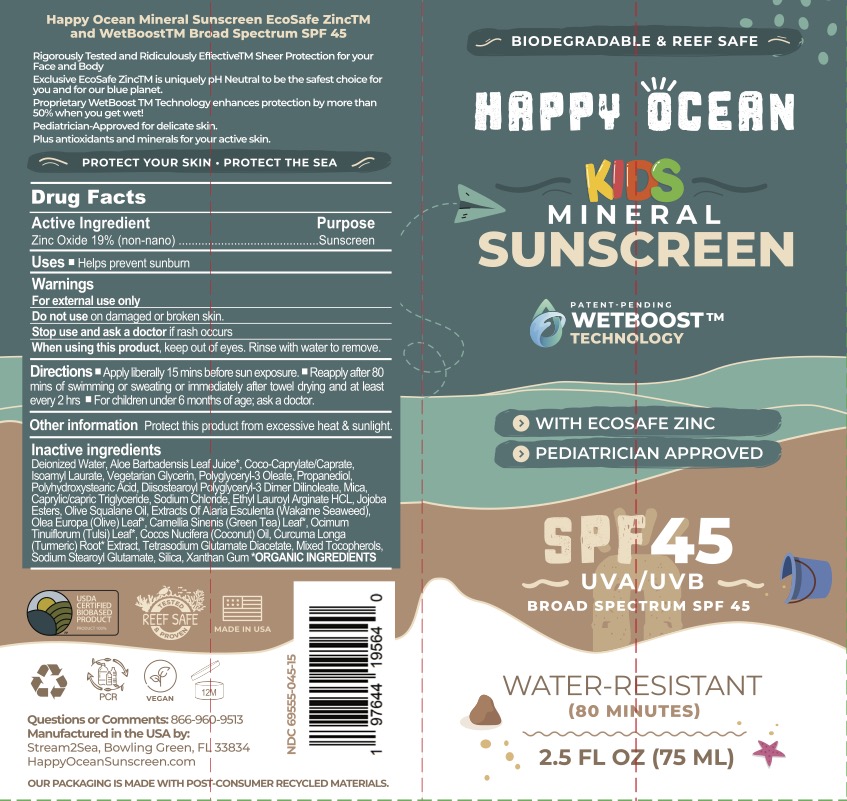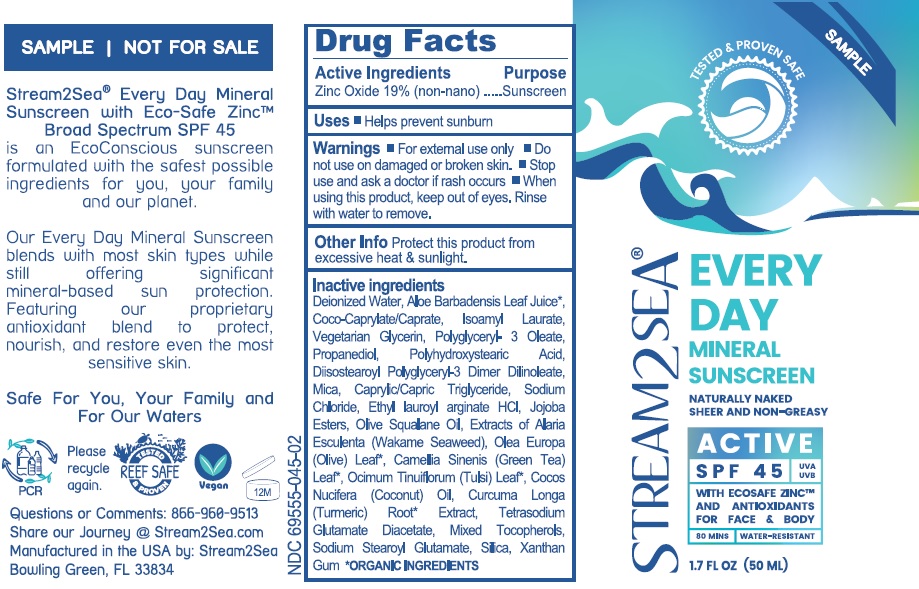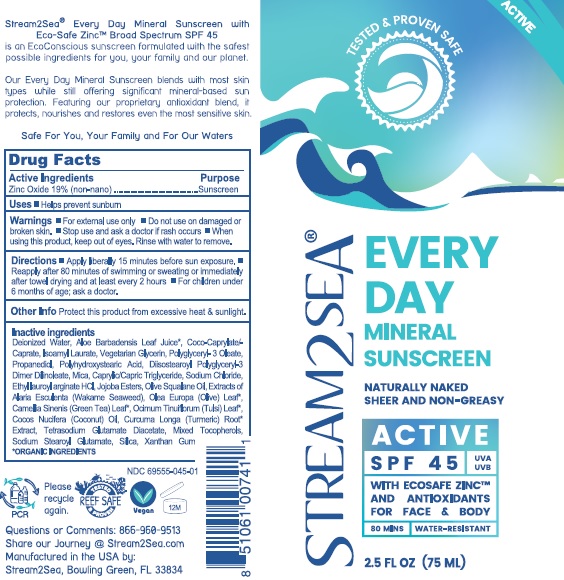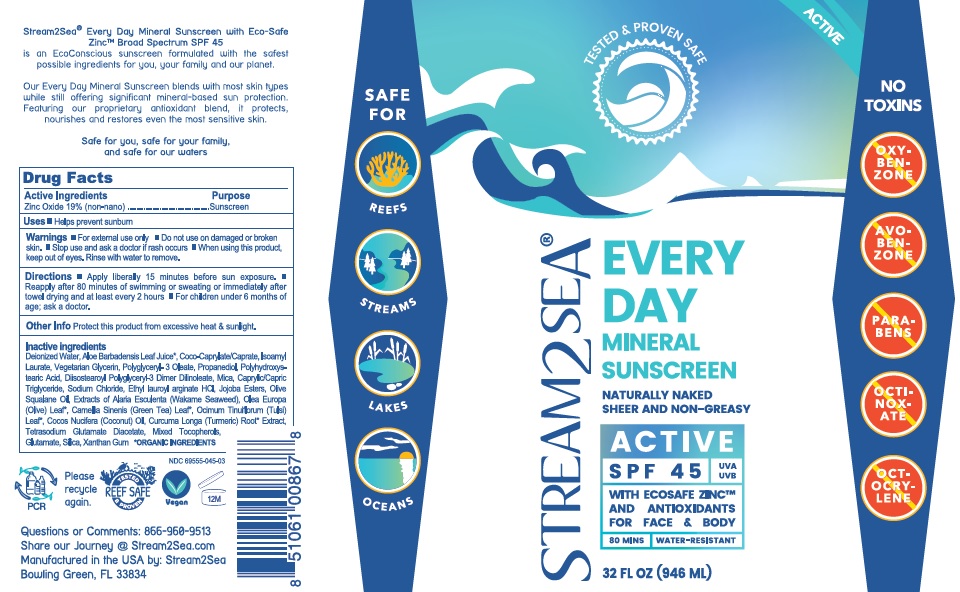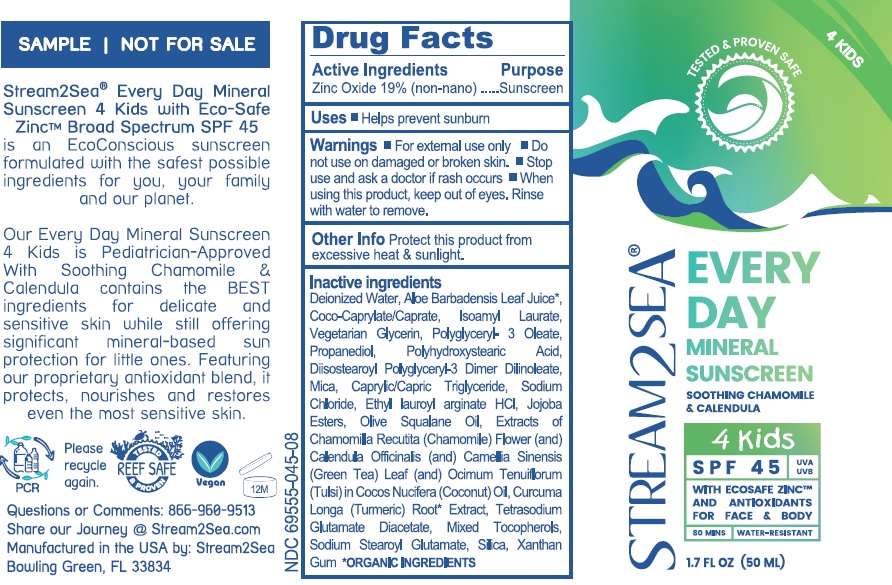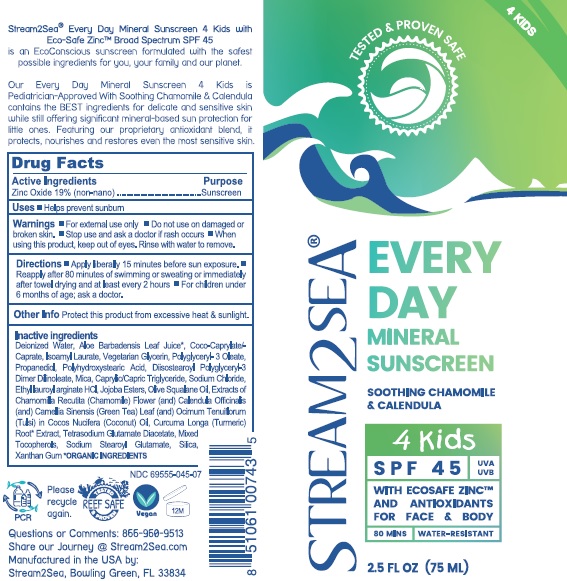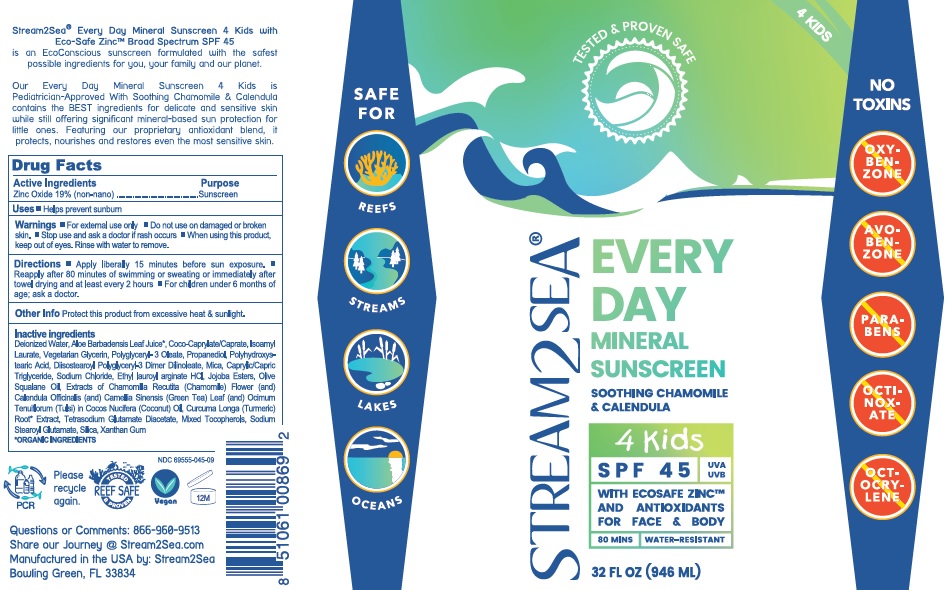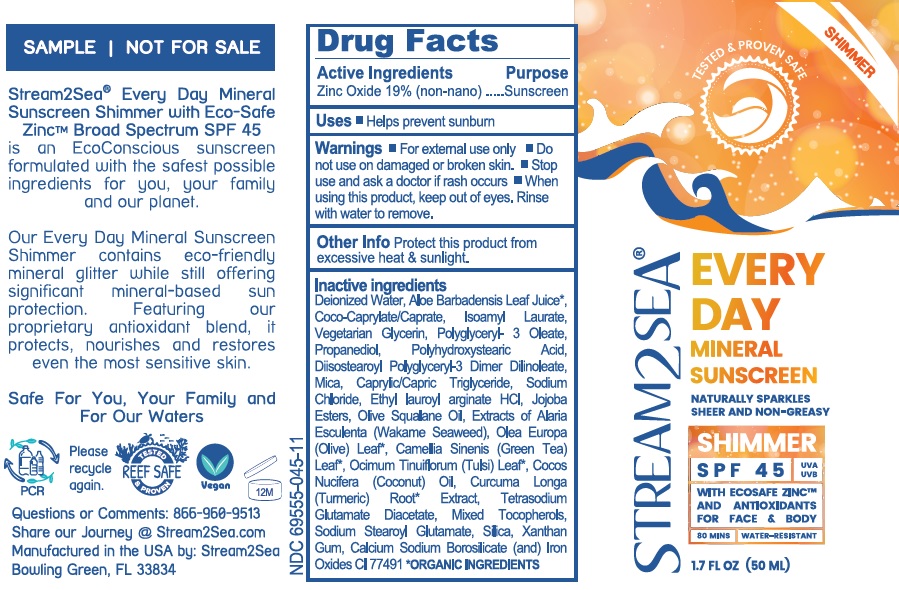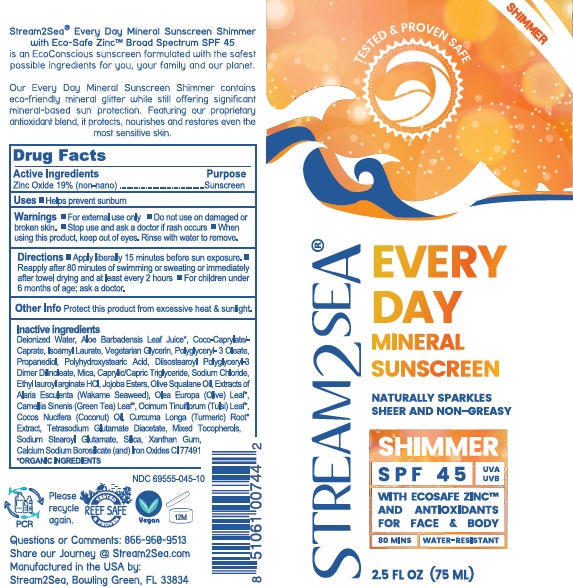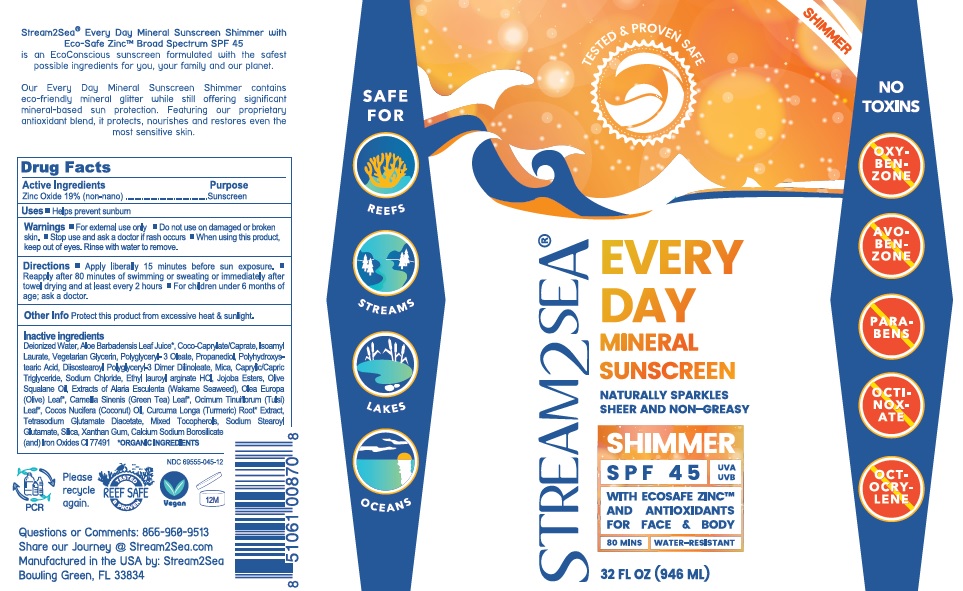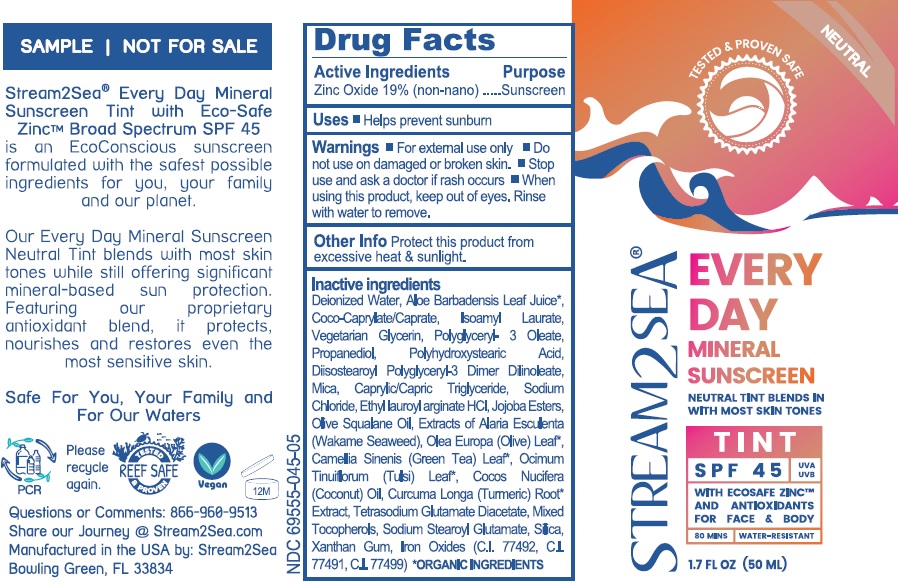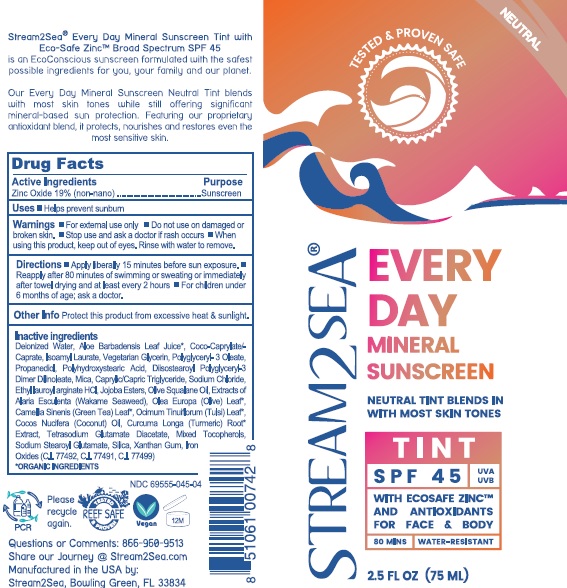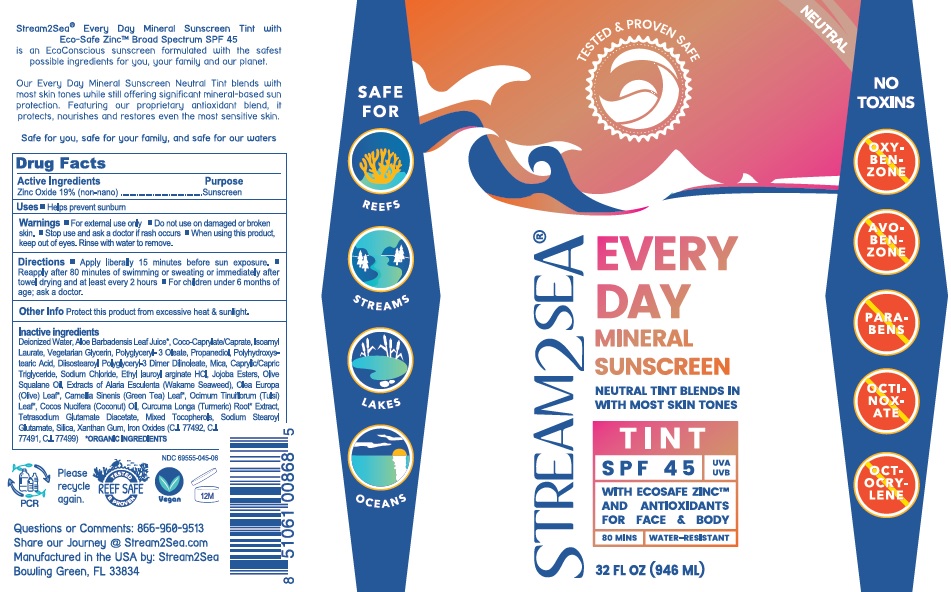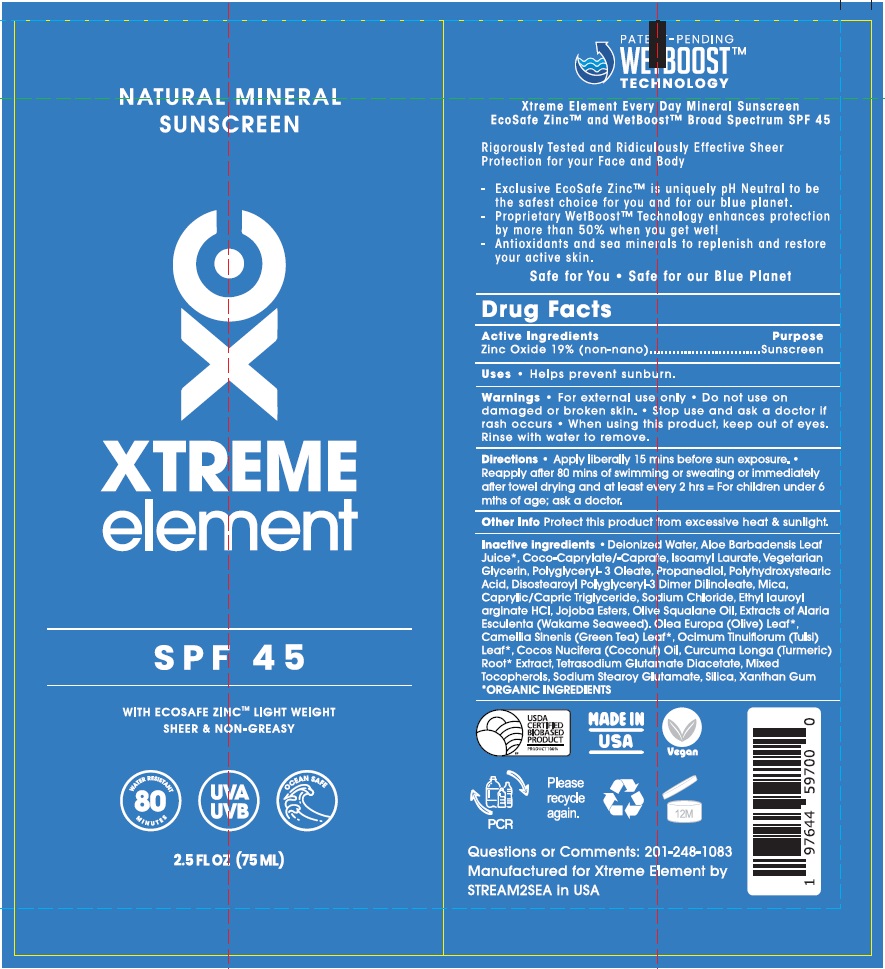 DRUG LABEL: EVERY DAY MINERAL SUN SCREEN SPF 45
NDC: 69555-045 | Form: CREAM
Manufacturer: Stream2Sea, LLC
Category: otc | Type: HUMAN OTC DRUG LABEL
Date: 20250504

ACTIVE INGREDIENTS: ZINC OXIDE 190 mg/1 mL
INACTIVE INGREDIENTS: WATER; ALOE VERA LEAF; COCO-CAPRYLATE; ISOAMYL LAURATE; GLYCERIN; POLYGLYCERYL-3 OLEATE; PROPANEDIOL; POLYHYDROXYSTEARIC ACID (2300 MW); DIISOSTEAROYL POLYGLYCERYL-3 DIMER DILINOLEATE; MICA; TRICAPRIN; SODIUM CHLORIDE; ETHYL LAUROYL ARGINATE HYDROCHLORIDE; HYDROLYZED JOJOBA ESTERS (ACID FORM); OLIVE OIL; ALARIA ESCULENTA; OLEA EUROPAEA LEAF; GREEN TEA LEAF; HOLY BASIL LEAF; COCONUT OIL; TURMERIC; TETRASODIUM GLUTAMATE DIACETATE; TOCOPHEROL; SODIUM STEAROYL GLUTAMATE; SILICON DIOXIDE; XANTHAN GUM; FERRIC OXIDE RED

EVERY DAY MINERAL SUN SCREEN SPF 45

Drug Facts

Active ingredients

Zinc Oxide 19% (Non-Nano)

Purpose
Sunscreen

Uses

- Helps prevent sunburn

Warnings

- For external use only.
- Do not use on damaged or broken skin.
- Stop use and ask a doctor if rash occurs.
- When using this product, keep out of eyes. Rinse with water to remove.

KEEP OUT OF REACH OF CHILDREN

If product is swallowed, get medical help or contact a Poison Control Center right away.

Directions

- Apply liberally 15 minutes before sun exposure.
- Reapply after 80 minutes of swimming or sweating or immediately after towel drying and at least every 2 hours.
- For children under 6 months of age; ask a doctor.

Other info

Protect this product from excessive heat & sunlight.

Inactive ingredients

Every Day Mineral Sun Screen Active SPF 45 (75mL, 50mL and 946mL) & Natural Mineral Sunscreen Extreme Elements SPF 45 (75mL)

Deionized Water, Aloe Barbadensis Leaf Juice*, Coco-Caprylate/Caprate, Isoamyl Laurate, Vegetarian Glycerin, Polyglyceryl- 3 Oleate, Propanediol, Polyhydroxystearic Acid, Diisostearoyl Polyglyceryl- 3 Dimer Dinoleate, Mica, Caprylic/Capric Triglyceride, Sodium Chloride, Ethyl lauroyl arginate HCl, Jojoba Esters, Olive Squalane Oil, Extracts of Alaria Esculenta (Wakame Seaweed), Olea Europa (Olive) Leaf*, Camellia Sinenis (Green Tea) Leaf*, Ocimum Tinuiflorum (Tulsi) Leaf*, Cocos Nucifera (Coconut) Oil, Curcuma Longa (Turmeric) Root* Extract, Tetrasodium Glutamate Diacetate, Mixed Tocopherols, Sodium Stearoyl Glutamate, Silica, Xanthan Gum.
*ORGANIC INGREDIENTS

Every Day Mineral Sun Screen Tint SPF 45 (75mL, 50mL and 946mL)

Deionized Water, Aloe Barbadensis Leaf Juice*, Coco-Caprylate/Caprate, Isoamyl Laurate, Vegetarian Glycerin, Polyglyceryl- 3 Oleate, Propanediol, Polyhydroxystearic Acid, Diisostearoyl Polyglyceryl- 3 Dimer Dinoleate, Mica, Caprylic/Capric Triglyceride, Sodium Chloride, Ethyl lauroyl arginate HCl, Jojoba Esters, Olive Squalane Oil, Extracts of Alaria Esculenta (Wakame Seaweed), Olea Europa (Olive) Leaf*, Camellia Sinenis (Green Tea) Leaf*, Ocimum Tinuiflorum (Tulsi) Leaf*, Cocos Nucifera (Coconut) Oil, Curcuma Longa (Turmeric) Root* Extract, Tetrasodium Glutamate Diacetate, Mixed Tocopherols, Sodium Stearoyl Glutamate, Silica, Xanthan Gum, Iron Oxides, (C.I.77492, C.I.77491, C.I.77499).
*ORGANIC INGREDIENTS

Every Day Mineral Sun Screen 4 Kids SPF 45 (75mL, 50mL and 946mL)

Deionized Water, Aloe Barbadensis Leaf Juice*, Coco-Caprylate/Caprate, Isoamyl Laurate, Vegetarian Glycerin, Polyglyceryl- 3 Oleate, Propanediol, Polyhydroxystearic Acid, Diisostearoyl Polyglyceryl- 3 Dimer Dinoleate, Mica, Caprylic/Capric Triglyceride, Sodium Chloride, Ethyl lauroyl arginate HCl, Jojoba Esters, Olive Squalane Oil, Extracts of Alaria Esculenta (Wakame Seaweed), Olea Europa (Olive) Leaf*, Camellia Sinenis (Green Tea) Leaf*, Ocimum Tinuiflorum (Tulsi) Leaf*, Cocos Nucifera (Coconut) Oil, Curcuma Longa (Turmeric) Root* Extract, Tetrasodium Glutamate Diacetate, Mixed Tocopherols, Sodium Stearoyl Glutamate, Silica, Xanthan Gum.
*ORGANIC INGREDIENTS

Every Day Mineral Sun Screen Shimmer SPF 45 (75mL, 50mL and 946mL)

Deionized Water, Aloe Barbadensis Leaf Juice*, Coco-Caprylate/Caprate, Isoamyl Laurate, Vegetarian Glycerin, Polyglyceryl- 3 Oleate, Propanediol, Polyhydroxystearic Acid, Diisostearoyl Polyglyceryl- 3 Dimer Dinoleate, Mica, Caprylic/Capric Triglyceride, Sodium Chloride, Ethyl lauroyl arginate HCl, Jojoba Esters, Olive Squalane Oil, Extracts of Alaria Esculenta (Wakame Seaweed), Olea Europa (Olive) Leaf*, Camellia Sinensis (Green Tea) Leaf*, Ocimum Tinuiflorum (Tulsi) Leaf*, Cocos Nucifera (Coconut) Oil, Curcuma Longa (Turmeric) Root* Extract, Tetrasodium Glutamate Diacetate, Mixed Tocopherols, Sodium Stearoyl Glutamate, Silica, Xanthan Gum, Calcium Sodium Borosilicate (and) Iron Oxides C.I.77492
*ORGANIC INGREDIENTS

Happy Ocean Mineral Sunscreen SPF 45 (75mL) and Happy Ocean Kids Mineral Sunscreen SPF 45 (75mL)

Deionized Water, Aloe Barbadensis Leaf Juice*, Coco-Caprylate/Caprate, Isoamyl Laurate, Vegetarian Glycerin, Polyglyceryl- 3 Oleate, Propanediol, Polyhydroxystearic Acid, Diisostearoyl Polyglyceryl- 3 Dimer Dinoleate, Mica, Caprylic/Capric Triglyceride, Sodium Chloride, Ethyl Lauroyl Arginate HCl, Jojoba Esters, Olive Squalane Oil, Extracts of Alaria Esculenta (Wakame Seaweed), Olea Europa (Olive) Leaf*, Camellia Sinensis (Green Tea) Leaf*, Ocimum Tinuiflorum (Tulsi) Leaf*, Cocos Nucifera (Coconut) Oil, Curcuma Longa (Turmeric) Root* Extract, Tetrasodium Glutamate Diacetate, Mixed Tocopherols, Sodium Stearoyl Glutamate, Silica, Xanthan Gum, Calcium Sodium Borosilicate (and) Iron Oxides C.I.77492

*ORGANIC INGREDIENTS

Makai Beauty SPF 45 Mineral Sunscreen (75mL) and Counting Coral Everyday Mineral Sunscreen SPF 45 (75mL)

Aloe Barbadensis Leaf Juice*, Caprylic/Capric Triglyceride, Coco-Caprylate/Caprate, Curcuma Longa (Turmeric) Root* Extract, Deionized Water, Diisostearoyl Polyglyceryl-3 Dimer Dilinoleate, Ethyl Lauroyl Arginate HCl, Hibiscus Sabdariffa Flower Extract, Chamomilla Recutita (Chamomile) Extract, Camellia Sinensis Leaf (White Tea) Extract, Alaria Esculenta (Wakame Seaweed) Extract, Camellia Sinensis (Green Tea) Leaf Extract*, Ocimum Tenuiflorum (Tulsi) Leaf Extract*, Olea Europaea (Olive) Leaf Extract* in Cocos Nucifera (Coconut) Oil, Isoamyl Laurate, Jojoba Esters, Mica, Mixed Tocopherols, Olive Squalane Oil, Polyglyceryl-3 Oleate, Polyhydroxystearic Acid, Propanediol, Silica, Sodium Chloride, Sodium Stearoyl glutamate, Tetrasodium Glutamate Diacetate, Vegetarian Glycerin, Xanthan Gum

*ORGANIC INGREDIENTS

Makai CC Cream

Deionized Water, Aqueous Extracts (Chamomile, Green Tea Leaf*, Hibiscus, Olive Leaf*, Tulsi Leaf*, Wakame Seaweed*), Caprylic/Capric Triglyceride, Aloe Leaf Juice, Cocoglycerides, Glycerin, Cetearyl Alcohol, Cetyl Palmitate, Polyhdroxystearic Acid, Sorbitan Olivate, Cetearyl Olivate, Methylcellulose, Olive Squalane Oil, Coconut Oil*, Stearic Acid, Acrylates Copolymer, Magnesium Aluminum Silicate, Sorbitan Palmitate, Tocopherol, Xanthan Gum, Alumina, Benzyl Alcohol, Salicylic Acid, Sorbic Acid, Iron Oxides (CI 77492, CI 77491, CI 77499), Jojoba Esters

*ORGANIC INGREDIENTS

PACKAGE LABEL.PRINCIPAL DISPLAY PANEL

EVERY DAY MINERAL SUNSCREEN ACTIVE SPF 45 (75mL) - LABEL

NATURAL MINERAL SUNSCREEN EXTREME ELEMENTS SPF 45

EVERY DAY MINERAL SUNSCREEN ACTIVE SPF 45 (50mL) - LABEL

EVERY DAY MINERAL SUNSCREEN ACTIVE SPF 45 (946mL) - LABEL

EVERY DAY MINERAL SUNSCREEN TINT SPF 45 (75mL) - LABEL

EVERY DAY MINERAL SUNSCREEN TINT SPF 45 (50mL) - LABEL

EVERY DAY MINERAL SUNSCREEN TINT SPF 45 (946mL) - LABEL

EVERY DAY MINERAL SUNSCREEN 4 KIDS SPF 45 (75mL) - LABEL

EVERY DAY MINERAL SUNSCREEN 4 KIDS SPF 45 (50mL) - LABEL

EVERY DAY MINERAL SUNSCREEN 4 KIDS SPF 45 (946mL) - LABEL

EVERY DAY MINERAL SUNSCREEN SHIMMER SPF 45 (75mL) - LABEL

EVERY DAY MINERAL SUNSCREEN SHIMMER SPF 45 (50mL) - LABEL

EVERY DAY MINERAL SUNSCREEN SHIMMER SPF 45 (946mL) - LABEL

HAPPY OCEAN MINERAL SUNSCREEN SPF 45 (75mL) - LABEL

HAPPY OCEAN KIDS MINERAL SUNSCREEN SPF 45 (75mL) - LABEL

MAKAI BEAUTY SPF 45 MINERAL SUNSCREEN, 75 ML - LABEL

Makai Beauty CC Cream SPF 45, 30mL - Label

Counting Coral Everyday Mineral Sunscreen SPF 45 (75mL)